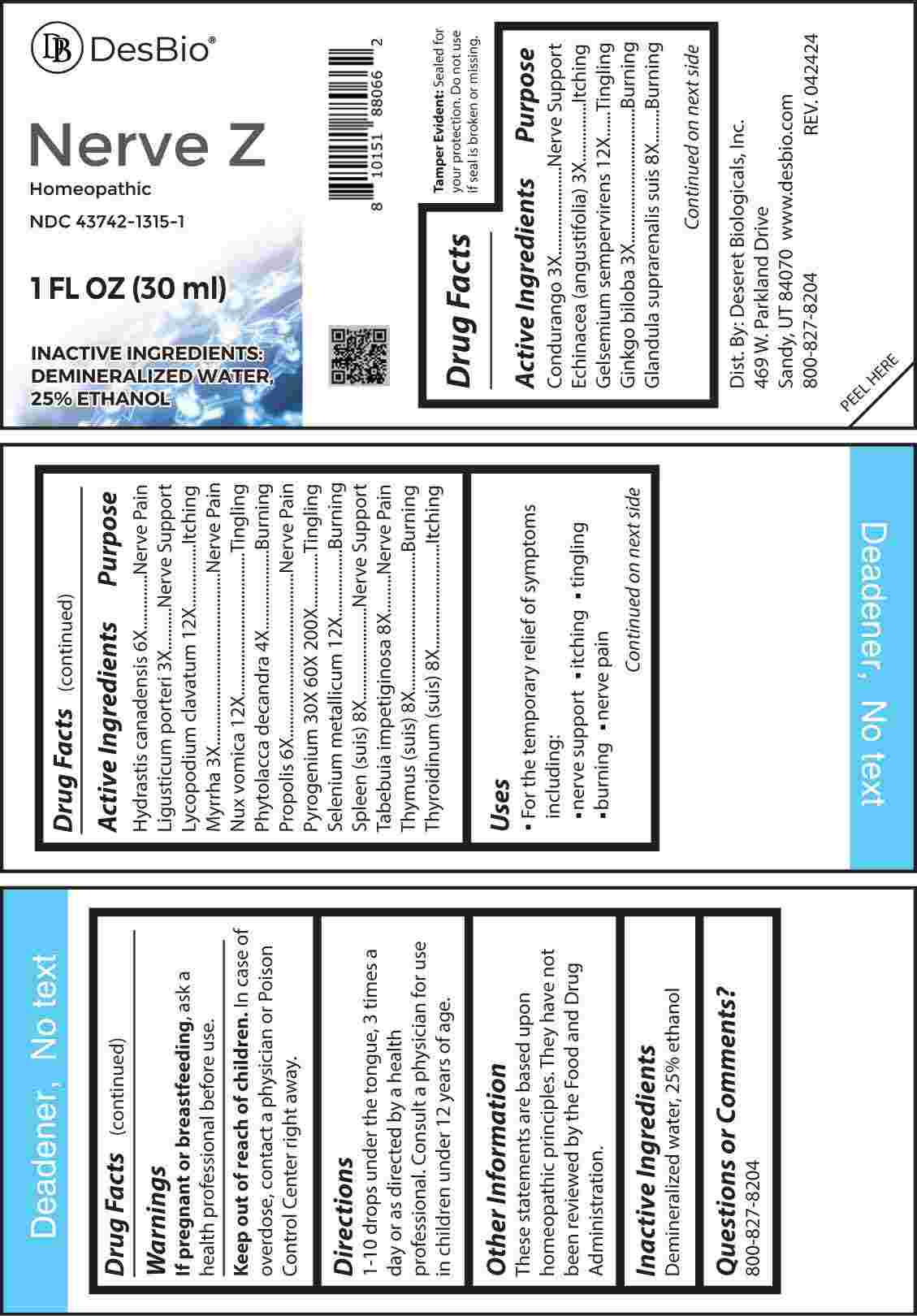 DRUG LABEL: Nerve Z
NDC: 43742-1315 | Form: LIQUID
Manufacturer: Deseret Biologicals, Inc.
Category: homeopathic | Type: HUMAN OTC DRUG LABEL
Date: 20240820

ACTIVE INGREDIENTS: MARSDENIA CONDURANGO BARK 3 [hp_X]/1 mL; ECHINACEA ANGUSTIFOLIA WHOLE 3 [hp_X]/1 mL; GINKGO 3 [hp_X]/1 mL; LIGUSTICUM PORTERI ROOT 3 [hp_X]/1 mL; MYRRH 3 [hp_X]/1 mL; PHYTOLACCA AMERICANA ROOT 4 [hp_X]/1 mL; GOLDENSEAL 6 [hp_X]/1 mL; PROPOLIS WAX 6 [hp_X]/1 mL; SUS SCROFA ADRENAL GLAND 8 [hp_X]/1 mL; SUS SCROFA SPLEEN 8 [hp_X]/1 mL; TABEBUIA IMPETIGINOSA BARK 8 [hp_X]/1 mL; THYROID 8 [hp_X]/1 mL; GELSEMIUM SEMPERVIRENS ROOT 12 [hp_X]/1 mL; LYCOPODIUM CLAVATUM SPORE 12 [hp_X]/1 mL; STRYCHNOS NUX-VOMICA SEED 12 [hp_X]/1 mL; SELENIUM 12 [hp_X]/1 mL; RANCID BEEF 30 [hp_X]/1 mL
INACTIVE INGREDIENTS: WATER; ALCOHOL

DRUG FACTS:

ACTIVE INGREDIENTS:

Condurango 3X, Echinacea (Angustifolia) 3X, Gelsemium Sempervirens 12X, Ginkgo Biloba 3X, Glandula Suprarenalis Suis 8X, Hydrastis Canadensis 6X, Ligusticum Porteri 3X, Lycopodium Clavatum 12X, Myrrha 3X, Nux Vomica 12X, Phytolacca Decandra 4X, Propolis 6X, Pyrogenium 30X, 60X, 200X, Selenium Metallicum 12X, Spleen (Suis) 8X, Tabebuia Impetiginosa 8X, Thymus (Suis) 8X, Thyroidinum (Suis) 8X.

PURPOSE:

Condurango – Nerve Support, Echinacea (Angustifolia) - Itching, Gelsemium Sempervirens - Tingling, Ginkgo Biloba - Burning, Glandula Suprarenalis Suis - Burning, Hydrastis Canadensis – Nerve Pain, Ligusticum Porteri – Nerve Support, Lycopodium Clavatum - Itching, Myrrha – Nerve Pain, Nux Vomica - Tingling, Phytolacca Decandra - Burning, Propolis – Nerve Pain, Pyrogenium - Tingling, Selenium Metallicum - Burning, Spleen (Suis) – Nerve Support, Tabebuia Impetiginosa – Nerve Pain, Thymus (Suis) - Burning, Thyroidinum (Suis) - Itching

USES:

• For the temporary relief of symptoms including:

• nerve support • itching • tingling • burning • nerve pain

These statements are based upon homeopathic principles. They have not been reviewed by the Food and Drug Administration.

WARNINGS:

If pregnant or breast-feeding, ask a health professional before use.

Keep out of reach of children. In case of overdose, contact a physician or Poison Control Center right away.

Tamper Evident: Sealed for your protection. Do not use if seal is broken or missing.

KEEP OUT OF REACH OF CHILDREN:

In case of overdose, contact a physician or Poison Control Center right away.

DIRECTIONS:

1-10 drops under the tongue, 3 times a day or as directed by a health professional. Consult a physician for use in children under 12 years of age.

INACTIVE INGREDIENTS:

Demineralized water, 25% ethanol

QUESTIONS:

Dist. By: Deseret Biologicals, Inc.
469 W. Parkland Drive
Sandy, UT 84070

www.desbio.com

800-827-8204

PACKAGE LABEL DISPLAY:

Des Bio

Nerve Z

Homeopathic

NDC 43742-1315-1

1 FL OZ (30 ml)